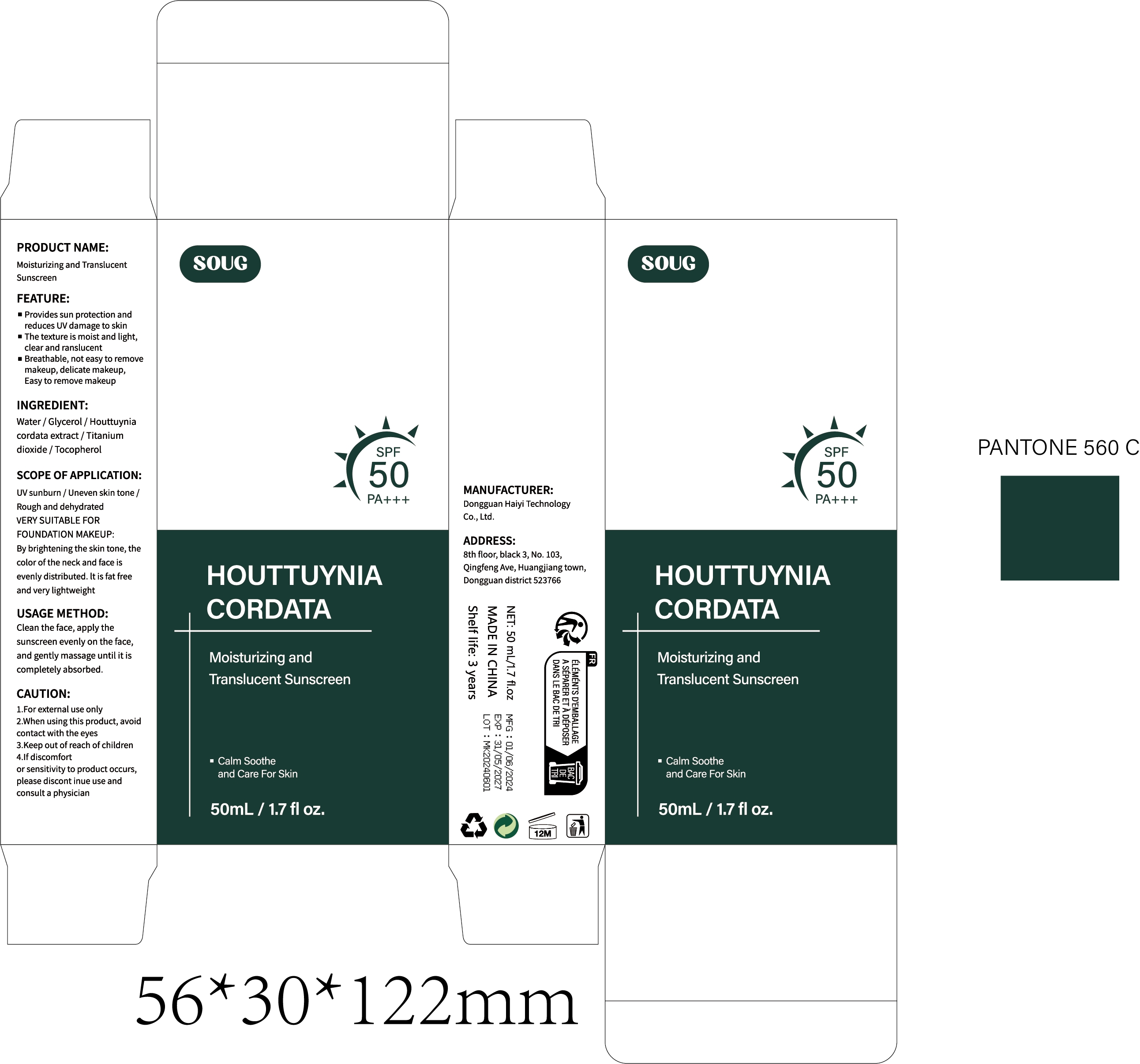 DRUG LABEL: Moisturizing and Translucent Sunscreen
NDC: 85594-003 | Form: CREAM
Manufacturer: Dongguan Haiyi Cosmetics Co., Ltd.
Category: otc | Type: HUMAN OTC DRUG LABEL
Date: 20250511

ACTIVE INGREDIENTS: HOUTTUYNIA CORDATA WHOLE 6 mg/100 mL
INACTIVE INGREDIENTS: TITANIUM DIOXIDE; GLYCERIN; TOCOPHEROL; WATER

85594-003-01 Moisturizing and Translucent Sunscreen

ACTIVE INGREDIENT

Houttuynia cordata extract

INACTIVE INGREDIENT

Water / Glycerol / Houttuynia cordata extract /Titanium dioxide / Tocopherol

PURPOSE

■ Provides sun protection and reduces UV damage to skin
■ The texture is moist and light,clear andranslucent
■Breathable, not easy to remove makeup, delicate makeup, Easy to remove makeup

WARNINGS

1.For external use only

2.When using this product, avoidcontact with the eyes

STOP USE

lf discomfortor sensitivity to product occurs,please discont inue use and consult a physician

DO NOT USE

Not suitable for use by children, pregnantor breast feeding people.

KEEP OUT OF REACH OF CHILDREN

KEEP THE PRODUCT OUT OF REACH OF CHILDREN to

INDICATIONS AND USAGE

Clean the face, apply the sunscreen evenly on the face,and gently massage until it is completely absorbed.

DOSAGE AND ADMINISTRATION

Apply an adequate amount (about a coin-sized portion or 2mg/cm²) evenly to the face and neck.